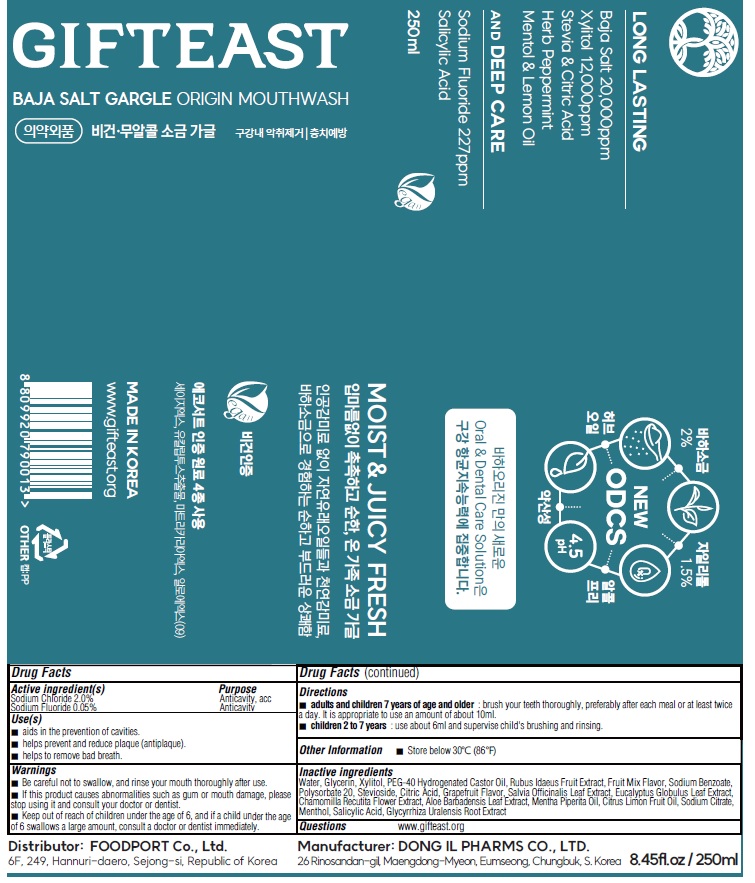 DRUG LABEL: GIFTEAST BAJA SALT GARGLE ORIGIN
NDC: 83445-010 | Form: MOUTHWASH
Manufacturer: FOODPORT
Category: otc | Type: HUMAN OTC DRUG LABEL
Date: 20230517

ACTIVE INGREDIENTS: Sodium Fluoride 0.05 g/100 mL; Sodium Chloride 2.0 g/100 mL
INACTIVE INGREDIENTS: WATER; Glycerin; Xylitol

Active ingredient(s)

Sodium Fluoride 0.05%
Sodium Chloride 2.0%

Inactive ingredients

Water, Glycerin, Xylitol, PEG-40 Hydrogenated Castor Oil, Rubus Idaeus Fruit Extract, Fruit Mix Flavor, Sodium Benzoate, Polysorbate 20, Stevioside, Citric Acid, Grapefruit Flavor, Salvia Officinalis Leaf Extract, Eucalyptus Globulus Leaf Extract, Chamomilla Recutita Flower Extract, Aloe Barbadensis Leaf Extract, Mentha Piperita Oil, Citrus Limon Fruit Oil, Sodium Citrate, Menthol, Salicylic Acid, Glycyrrhiza Uralensis Root Extract

Purpose

Anticavity
Anticavity, acc

WARNINGS

■ Be careful not to swallow, and rinse your mouth thoroughly after use.
■ If this product causes abnormalities such as gum or mouth damage, please stop using it and consult your doctor or dentist.
■ Keep out of reach of children under the age of 6, and if a child under the age of 6 swallows a large amount, consult a doctor or dentist immediately.

■ Keep out of reach of children under the age of 6, and if a child under the age of 6 swallows a large amount, consult a doctor or dentist immediately.

Use(s)

■ aids in the prevention of cavities.
■ helps prevent and reduce plaque (antiplague).
■ helps to remove bad breath.

Directions

■ adults and children 7 years of age and older : brush your teeth thoroughly, preferably after each meal or at least twice a day.
It is appropriate to use an amount of about 10ml
■ children 2 to 7 years : use about 6ml and supervise child's brushing and rinsing

Other Information

■ Store below 30℃(86℉)

Questions

www.gifteast.org